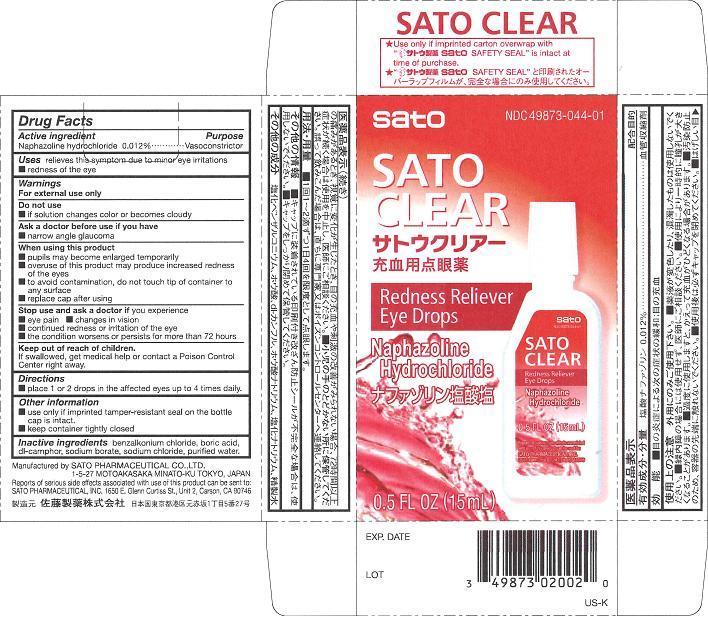 DRUG LABEL: Sato Clear
NDC: 49873-044 | Form: SOLUTION/ DROPS
Manufacturer: Sato Pharmaceutical Co., Ltd.
Category: otc | Type: HUMAN OTC DRUG LABEL
Date: 20231128

ACTIVE INGREDIENTS: NAPHAZOLINE HYDROCHLORIDE 12 mg/100 mL
INACTIVE INGREDIENTS: CAMPHOR (SYNTHETIC); BENZALKONIUM CHLORIDE; SODIUM CHLORIDE; BORIC ACID; SODIUM BORATE; WATER

Sato Clear

Active ingredient
Naphazoline hydrochloride 0.012%

Purpose
Naphazoline hydrochloride Vasoconstrictor

INDICATIONS AND USAGE

Uses relieves this symptom due to minor eye irritations
■ redness of the eye

Warnings

For external use only

Do not use

- if solution changes color or becomes cloudy

Ask a doctor before use if you have

- narrow angle glaucoma

When using this product

- pupils may become enlarged temporarily
- overuse of this product may produce increased redness of the eyes
- to avoid contamination, do not touch tip of container to any surface
- replace cap after using

Stop use and ask a doctor if you experience

- eye pain
- changes in vision
- continued redness or irritation of the eye
- the condition worsens or persists for more than 72 hours

Keep out of reach of children.
If swallowed, get medical help or contact a Poison Control Center right away.

Directions
■ Place 1 or 2 drops in the affected eyes up to 4 times daily.

Other information

- use only if imprinted tamper-resistant seal on the bottle cap is intact
- keep container tightly closed

INACTIVE INGREDIENT

Inactive ingredients benzalkonium chloride, boric acid, dl-camphor, sodium borate, sodium chloride, purified water.